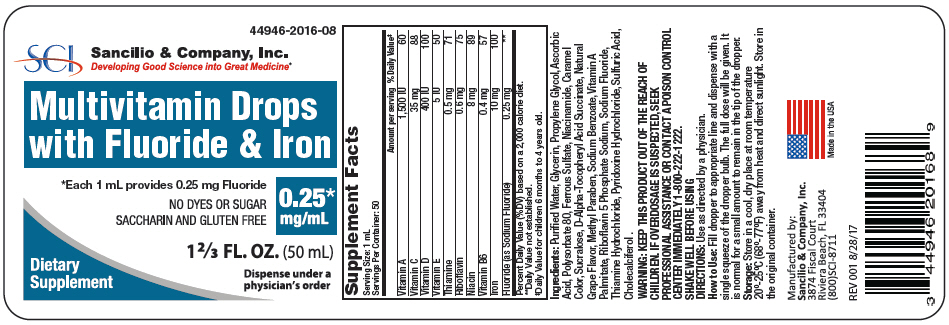 DRUG LABEL: MultiVitamin Drops with Fluoride and Iron
NDC: 44946-2016 | Form: LIQUID
Manufacturer: Sancilio & Company, Inc.
Category: other | Type: DIETARY SUPPLEMENT
Date: 20180411

ACTIVE INGREDIENTS: Vitamin A Palmitate 1500 [iU]/1 mL; Ascorbic Acid 35 mg/1 mL; CHOLECALCIFEROL 400 [iU]/1 mL; TOCOPHEROL 5 [iU]/1 mL; THIAMINE HYDROCHLORIDE 0.5 mg/1 mL; RIBOFLAVIN 5'-PHOSPHATE SODIUM 0.6 mg/1 mL; NIACINAMIDE 8 mg/1 mL; PYRIDOXINE HYDROCHLORIDE 0.4 mg/1 mL; FERROUS SULFATE 10 mg/1 mL; Sodium Fluoride 0.25 mg/1 mL
INACTIVE INGREDIENTS: WATER; Glycerin; Propylene Glycol; Polysorbate 80; Sucralose; Methylparaben; Caramel; Sodium Benzoate; Sulfuric Acid

Multivitamin Drops with Fluoride & Iron

STATEMENT OF IDENTITY

Supplement Facts
Serving Size: 1 mL
Servings Per Container: 50
 | Amount per serving | % Daily Value [Daily Value for children 6 months to 4 years old.]
Vitamin A | 1,500 IU | 60
Vitamin C | 35 mg | 88
Vitamin D | 400 IU | 100
Vitamin E | 5 IU | 50
Thiamine | 0.5 mg | 71
Riboflavin | 0.6 mg | 75
Niacin | 8 mg | 89
Vitamin B6 | 0.4 mg | 57
Iron | 10 mg | 100
Fluoride (as Sodium Fluoride) | 0.25 mg | [Daily Value not established.]
Percent Daily Value (%DV) based on a 2,000 calorie diet.

Ingredients: Purified Water, Glycerin, Propylene Glycol, Ascorbic Acid, Polysorbate 80, Ferrous Sulfate, Niacinamide, Caramel Color, Sucralose, D-Alpha-Tocopheryl Acid Succinate, Natural Grape Flavor, Methyl Paraben, Sodium Benzoate, Vitamin A Palmitate, Riboflavin 5 Phosphate Sodium, Sodium Fluoride, Thiamine Hydrochloride, Pyridoxine Hydrochloride, Sulfuric Acid, Cholecalciferol .

WARNING

KEEP THIS PRODUCT OUT OF THE REACH OF CHILDREN. IF OVERDOSAGE IS SUSPECTED, SEEK PROFESSIONAL ASSISTANCE OR CONTACT A POISON CONTROL CENTER IMMEDIATELY 1-800-222-1222.

SHAKE WELL BEFORE USING

DIRECTIONS

Use as directed by a physician.

How to Use

Fill dropper to appropriate line and dispense with a single squeeze of the dropper bulb. The full dose will be given. It is normal for a small amount to remain in the tip of the dropper.

Storage

Store in a cool, dry place at room temperature 20°-25°C (68°-77°F) away from heat and direct sunlight. Store in the original container.

HEALTH CLAIM

Manufactured by:
Sancilio & Company, Inc.
3874 Fiscal Court
Riviera Beach, FL 33404
(800)SCI-8711

Made in the USA

REV 001 8/28/17

PRINCIPAL DISPLAY PANEL - 0.25 mg/mL Bottle Label

44946-2016-08

SCI
Sancilio & Company, Inc.
Developing Good Science into Great Medicine®

Multivitamin Drops
with Fluoride & Iron

*Each 1 mL provides 0.25 mg Fluoride

NO DYES OR SUGAR
SACCHARIN AND GLUTEN FREE

0.25*
mg/mL

1 ⅔ FL. OZ. (50 mL)

Dietary
Supplement

Dispense under a
physician's order